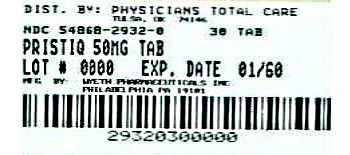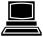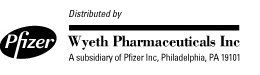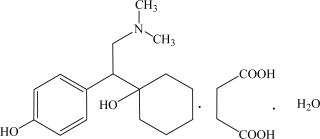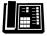 DRUG LABEL: Pristiq
NDC: 54868-2932 | Form: TABLET, EXTENDED RELEASE
Manufacturer: Physicians Total Care, Inc.
Category: prescription | Type: HUMAN PRESCRIPTION DRUG LABEL
Date: 20121026

ACTIVE INGREDIENTS: DESVENLAFAXINE SUCCINATE 50 mg/1 1
INACTIVE INGREDIENTS: CELLULOSE, MICROCRYSTALLINE; TALC; MAGNESIUM STEARATE; POLYETHYLENE GLYCOLS; TITANIUM DIOXIDE; FERRIC OXIDE RED; POLYVINYL ALCOHOL; FERRIC OXIDE YELLOW; HYPROMELLOSE 2208 (15000 MPA.S)

HIGHLIGHTS OF PRESCRIBING INFORMATION

These highlights do not include all the information needed to use PRISTIQ safely and effectively.
See full prescribing information for PRISTIQ.
PRISTIQ® (desvenlafaxine) Extended-Release Tablets, oral
Initial U.S. Approval: 2008

WARNING: SUICIDALITY AND ANTIDEPRESSANT DRUGS

See full prescribing information for complete boxed warning.

Increased risk of suicidal thinking and behavior in children, adolescents and young adults taking antidepressants for major depressive disorder (MDD) and other psychiatric disorders. PRISTIQ is not approved for use in pediatric patients (5.1).

1 INDICATIONS AND USAGE

PRISTIQ, a selective serotonin and norepinephrine reuptake inhibitor (SNRI), is indicated for the treatment of major depressive disorder [MDD] (1).

2 DOSAGE AND ADMINISTRATION

- Recommended dose: 50 mg once daily with or without food (2.1).
- There was no evidence that doses greater than 50 mg/day confer any additional benefit (2.1).
- When discontinuing treatment, gradual dose reduction is recommended whenever possible (2.1 and 5.9).
- Tablets should be taken whole; do not divide, crush, chew, or dissolve (2.1).
- Renal Impairment: The recommended dose in patients with moderate renal impairment is 50 mg/day. The recommended dose in patients with severe renal impairment and end-stage renal disease (ESRD) is 50 mg every other day. The dose should not be escalated in patients with moderate or severe renal impairment or ESRD (2.2).
- Hepatic Impairment: Dose escalation above 100 mg/day is not recommended (2.2).

3 DOSAGE FORMS AND STRENGTHS

- PRISTIQ tablets are available as 50 and 100 mg tablets (3).
- Each tablet contains 76 mg or 152 mg of desvenlafaxine succinate equivalent to 50 mg or 100 mg of desvenlafaxine (3).

4 CONTRAINDICATIONS

- Hypersensitivity to desvenlafaxine succinate, venlafaxine hydrochloride or any excipients in the PRISTIQ formulation (4.1).
- Do not use with an MAOI or within 14 days of stopping an MAOI. Allow 7 days after stopping PRISTIQ before starting an MAOI (4.2).

5 WARNINGS AND PRECAUTIONS

- Clinical Worsening/Suicide Risk: Monitor for clinical worsening and suicide risk (5.1).
- Serotonin Syndrome or Neuroleptic Malignant Syndrome (NMS)-like Reactions: Serotonin syndrome or NMS-like reactions have been reported with SSRIs and SNRIs. Discontinue PRISTIQ and initiate supportive treatment (5.2).
- Elevated Blood Pressure: Has occurred with PRISTIQ. Hypertension should be controlled before initiating treatment. Monitor blood pressure regularly during treatment (5.3).
- Abnormal Bleeding: PRISTIQ may increase the risk of bleeding events. Patients should be cautioned about the risk of bleeding associated with the concomitant use of PRISTIQ and NSAIDs, aspirin, or other drugs that affect coagulation (5.4).
- Narrow-angle Glaucoma: Mydriasis has occurred with PRISTIQ. Patients with raised intraocular pressure or those at risk of angle-closure glaucoma should be monitored (5.5).
- Activation of Mania/Hypomania: Has occurred. Use cautiously in patients with Bipolar Disorder. Caution patients about the risk of activation of mania/hypomania (5.6).
- Cardiovascular/Cerebrovascular Disease: Use cautiously in patients with cardiovascular or cerebrovascular disease (5.7).
- Cholesterol and Triglyceride Elevation: Have occurred. Use cautiously in patients with lipid metabolism disorders. Consider monitoring serum cholesterol and triglyceride (5.8).
- Discontinuation Symptoms: Have occurred. Taper the dose when possible and monitor for discontinuation symptoms (5.9).
- Renal Impairment: Reduces the clearance of PRISTIQ. Dosage adjustment is necessary in severe and ESRD. In moderate renal impairment, the dose should not exceed 50 mg/day (5.10).
- Seizure: Can occur. Use cautiously in patients with seizure disorder (5.11).
- Hyponatremia: Can occur in association with SIADH (5.12).
- Drugs Containing Desvenlafaxine or Venlafaxine: Should not be used concomitantly with PRISTIQ (5.13).
- Interstitial Lung Disease and Eosinophilic Pneumonia: Can occur (5.14).

6 ADVERSE REACTIONS

Adverse reactions in patients in short-term fixed-dose studies (incidence ≥ 5% and twice the rate of placebo in the 50 or 100 mg dose groups) were: nausea, dizziness, insomnia, hyperhidrosis, constipation, somnolence, decreased appetite, anxiety, and specific male sexual function disorders (6.1).

To report SUSPECTED ADVERSE REACTIONS, contact Wyeth Pharmaceuticals Inc., a subsidiary of Pfizer Inc., at 1-800-934-5556 or FDA at 1-800-FDA-1088 or www.fda.gov/medwatch

8 USE IN SPECIFIC POPULATIONS

- Dosage adjustment is recommended in patients with severe renal impairment and end-stage renal disease. The dose should not be escalated in moderate to severe impairment or in ESRD (2.2, 8.6 and 12.6).
- There is an increased incidence of orthostatic hypotension in PRISTIQ treated patients ≥ 65 years (6.1 and 8.5).
- For elderly patients, the possibility of reduced renal clearance of desvenlafaxine should be considered when determining dose (2.2).
- Only administer PRISTIQ to pregnant or breastfeeding women if the expected benefits outweigh the possible risks (8.1 and 8.3).

FULL PRESCRIBING INFORMATION

WARNING: SUICIDALITY AND ANTIDEPRESSANT DRUGS

Antidepressants increased the risk compared to placebo of suicidal thinking and behavior (suicidality) in children, adolescents, and young adults in short-term studies of Major Depressive Disorder (MDD) and other psychiatric disorders. Anyone considering the use of PRISTIQ® or any other antidepressant in a child, adolescent, or young adult must balance this risk with the clinical need. Short-term studies did not show an increase in the risk of suicidality with antidepressants compared to placebo in adults beyond age 24; there was a reduction in risk with antidepressants compared to placebo in adults aged 65 and older. Depression and certain other psychiatric disorders are themselves associated with increases in the risk of suicide. Patients of all ages who are started on antidepressant therapy should be monitored appropriately and observed closely for clinical worsening, suicidality, or unusual changes in behavior. Families and caregivers should be advised of the need for close observation and communication with the prescriber. PRISTIQ is not approved for use in pediatric patients [see Warnings and Precautions (5.1), Use in Specific Populations (8.4), and Patient Counseling Information (17.1)].

1 INDICATIONS AND USAGE

PRISTIQ, a selective serotonin and norepinephrine reuptake inhibitor (SNRI), is indicated for the treatment of major depressive disorder (MDD) [see Clinical Studies (14) and Dosage and Administration (2.1)]. The efficacy of PRISTIQ has been established in four 8-week, placebo-controlled studies of outpatients who met DSM-IV criteria for major depressive disorder.

A major depressive episode (DSM-IV) implies a prominent and relatively persistent (nearly every day for at least 2 weeks) depressed or dysphoric mood that usually interferes with daily functioning, and includes at least 5 of the following 9 symptoms: depressed mood, loss of interest in usual activities, significant change in weight and/or appetite, insomnia or hypersomnia, psychomotor agitation or retardation, increased fatigue, feelings of guilt or worthlessness, slowed thinking or impaired concentration, or a suicide attempt or suicidal ideation.

2 DOSAGE AND ADMINISTRATION

2.1 Initial Treatment of Major Depressive Disorder

The recommended dose for PRISTIQ is 50 mg once daily, with or without food.

In clinical studies, doses of 50-400 mg/day were shown to be effective, although no additional benefit was demonstrated at doses greater than 50 mg/day and adverse events and discontinuations were more frequent at higher doses.

When discontinuing therapy, gradual dose reduction is recommended whenever possible to minimize discontinuation symptoms [see Dosage and Administration (2.4) and Warnings and Precautions (5.9)].

PRISTIQ should be taken at approximately the same time each day. Tablets must be swallowed whole with fluid and not divided, crushed, chewed, or dissolved.

2.2 Special Populations

Pregnant women during the third trimester

Neonates exposed to SNRIs or SSRIs late in the third trimester have developed complications requiring prolonged hospitalization, respiratory support, and tube feeding [see Use in Specific Populations (8.1)]. When treating pregnant women with PRISTIQ during the third trimester, the physician should carefully consider the potential risks and benefits of treatment. The physician may consider tapering PRISTIQ in the third trimester.

Patients with renal impairment

No dosage adjustment is necessary in patients with mild renal impairment (24-hr CrCl = 50-80 mL/min).

The recommended dose in patients with moderate renal impairment (24-hr CrCl = 30-50 mL/min) is 50 mg per day. The recommended dose in patients with severe renal impairment (24-hr CrCl < 30 mL/min) or end-stage renal disease (ESRD) is 50 mg every other day. Supplemental doses should not be given to patients after dialysis. The doses should not be escalated in patients with moderate or severe renal impairment, or ESRD [see Warnings and Precautions (5.10), Use in Specific Populations (8.6) and Clinical Pharmacology (12.6)].

Patients with hepatic impairment

The recommended dose in patients with hepatic impairment is 50 mg/day. Dose escalation above 100 mg/day is not recommended [see Clinical Pharmacology (12.6)].

Elderly patients

No dosage adjustment is required solely on the basis of age; however, the possibility of reduced renal clearance of PRISTIQ should be considered when determining the dose [see Use in Specific Populations (8.5) and Clinical Pharmacology (12.6)].

2.3 Maintenance/Continuation/Extended Treatment

It is generally agreed that acute episodes of major depressive disorder require several months or longer of sustained pharmacologic therapy. However, the longer-term efficacy of PRISTIQ at a dose of 50 mg/day that was effective in short-term, controlled studies has not been studied. Patients should be periodically reassessed to determine the need for continued treatment.

2.4 Discontinuing PRISTIQ

Symptoms associated with discontinuation of PRISTIQ, other SNRIs and SSRIs have been reported [see Warnings and Precautions (5.9)]. Patients should be monitored for these symptoms when discontinuing treatment. A gradual reduction in the dose rather than abrupt cessation is recommended whenever possible. If intolerable symptoms occur following a decrease in the dose or upon discontinuation of treatment, then resuming the previously prescribed dose may be considered. Subsequently, the physician may continue decreasing the dose, but at a more gradual rate.

2.5 Switching Patients From Other Antidepressants to PRISTIQ

Discontinuation symptoms have been reported when switching patients from other antidepressants, including venlafaxine, to PRISTIQ. Tapering of the initial antidepressant may be necessary to minimize discontinuation symptoms [see Contraindications (4.2)].

2.6 Switching Patients To or From a Monoamine Oxidase Inhibitor (MAOI)

At least 14 days must elapse between discontinuation of an MAOI and initiation of therapy with PRISTIQ. In addition, at least 7 days must be allowed after stopping PRISTIQ before starting an MAOI [see Contraindications (4.2)].

3 DOSAGE FORMS AND STRENGTHS

PRISTIQ® (desvenlafaxine) Extended-Release Tablets are available as 50 and 100 mg tablets.

50 mg, light pink, square pyramid tablet debossed with “W” over “50” on the flat side

100 mg, reddish-orange, square pyramid tablet debossed with “W” over “100” on the flat side

4 CONTRAINDICATIONS

4.1 Hypersensitivity

Hypersensitivity to desvenlafaxine succinate, venlafaxine hydrochloride or to any excipients in the PRISTIQ formulation.

4.2 Monoamine Oxidase Inhibitors

PRISTIQ must not be used concomitantly in patients taking monoamine oxidase inhibitors (MAOIs) or in patients who have taken MAOIs within the preceding 14 days due to the risk of serious, sometimes fatal, drug interactions with SNRI or SSRI treatment or with other serotonergic drugs. These interactions have been associated with symptoms that include tremor, myoclonus, diaphoresis, nausea, vomiting, flushing, dizziness, hyperthermia with features resembling neuroleptic malignant syndrome, seizures, rigidity, autonomic instability with possible rapid fluctuations of vital signs, and mental status changes that include extreme agitation progressing to delirium and coma. Based on the half-life of desvenlafaxine, at least 7 days should be allowed after stopping PRISTIQ before starting an MAOI [see Dosage and Administration (2.6)].

5 WARNINGS AND PRECAUTIONS

5.1 Clinical Worsening and Suicide Risk

Patients with major depressive disorder (MDD), both adult and pediatric, may experience worsening of their depression and/or the emergence of suicidal ideation and behavior (suicidality) or unusual changes in behavior, whether or not they are taking antidepressant medications, and this risk may persist until significant remission occurs. Suicide is a known risk of depression and certain other psychiatric disorders, and these disorders themselves are the strongest predictors of suicide. There has been a long-standing concern, however, that antidepressants may have a role in inducing worsening of depression and the emergence of suicidality in certain patients during the early phases of treatment. Pooled analyses of short-term placebo-controlled studies of antidepressant drugs (SSRIs and others) showed that these drugs increase the risk of suicidal thinking and behavior (suicidality) in children, adolescents, and young adults (ages 18-24) with major depressive disorder (MDD) and other psychiatric disorders. Short-term studies did not show an increase in the risk of suicidality with antidepressants compared to placebo in adults beyond age 24; there was a reduction with antidepressants compared to placebo in adults aged 65 and older.

The pooled analyses of placebo-controlled studies in children and adolescents with MDD, obsessive compulsive disorder (OCD), or other psychiatric disorders included a total of 24 short-term studies of 9 antidepressant drugs in over 4,400 patients. The pooled analyses of placebo-controlled studies in adults with MDD or other psychiatric disorders included a total of 295 short-term studies (median duration of 2 months) of 11 antidepressant drugs in over 77,000 patients. There was considerable variation in risk of suicidality among drugs, but a tendency toward an increase in the younger patients for almost all drugs studied. There were differences in absolute risk of suicidality across the different indications, with the highest incidence in MDD. The risk differences (drug vs. placebo), however, were relatively stable within age strata and across indications. These risk differences (drug-placebo difference in the number of cases of suicidality per 1000 patients treated) are provided in Table 1.

Table 1
Age Range | Drug-Placebo Difference in Number of Cases of Suicidality per 1000 Patients Treated
 | Increases Compared to Placebo
<18 | 14 additional cases
18-24 | 5 additional cases
 | Decreases Compared to Placebo
25-64 | 1 fewer case
≥65 | 6 fewer cases

No suicides occurred in any of the pediatric studies. There were suicides in the adult studies, but the number was not sufficient to reach any conclusion about drug effect on suicide.

It is unknown whether the suicidality risk extends to longer-term use, i.e., beyond several months. However, there is substantial evidence from placebo-controlled maintenance studies in adults with depression that the use of antidepressants can delay the recurrence of depression.

All patients being treated with antidepressants for any indication should be monitored appropriately and observed closely for clinical worsening, suicidality, and unusual changes in behavior, especially during the initial few months of a course of drug therapy, or at times of dose changes, either increases or decreases.

The following symptoms, anxiety, agitation, panic attacks, insomnia, irritability, hostility, aggressiveness, impulsivity, akathisia (psychomotor restlessness), hypomania, and mania, have been reported in adult and pediatric patients being treated with antidepressants for major depressive disorder as well as for other indications, both psychiatric and nonpsychiatric. Although a causal link between the emergence of such symptoms and either the worsening of depression and/or the emergence of suicidal impulses has not been established, there is concern that such symptoms may represent precursors to emerging suicidality.

Consideration should be given to changing the therapeutic regimen, including possibly discontinuing the medication, in patients whose depression is persistently worse, or who are experiencing emergent suicidality or symptoms that might be precursors to worsening depression or suicidality, especially if these symptoms are severe, abrupt in onset, or were not part of the patient's presenting symptoms.

If the decision has been made to discontinue treatment, medication should be tapered, as rapidly as is feasible, but with recognition that abrupt discontinuation can be associated with certain symptoms [see Warnings and Precautions (5.9) and Dosage and Administration (2.3) for a description of the risks of discontinuation of PRISTIQ].

Families and caregivers of patients being treated with antidepressants for major depressive disorder or other indications, both psychiatric and nonpsychiatric, should be alerted about the need to monitor patients for the emergence of agitation, irritability, unusual changes in behavior, and the other symptoms described above, as well as the emergence of suicidality, and to report such symptoms immediately to healthcare providers. Such monitoring should include daily observation by families and caregivers. Prescriptions for PRISTIQ should be written for the smallest quantity of tablets consistent with good patient management, in order to reduce the risk of overdose.

Screening patients for bipolar disorder

A major depressive episode may be the initial presentation of bipolar disorder. It is generally believed (though not established in controlled studies) that treating such an episode with an antidepressant alone may increase the likelihood of precipitation of a mixed/manic episode in patients at risk for bipolar disorder. Whether any of the symptoms described above represent such a conversion is unknown. However, prior to initiating treatment with an antidepressant, patients with depressive symptoms should be adequately screened to determine if they are at risk for bipolar disorder; such screening should include a detailed psychiatric history, including a family history of suicide, bipolar disorder, and depression. It should be noted that PRISTIQ is not approved for use in treating bipolar depression.

5.2 Serotonin Syndrome or Neuroleptic Malignant Syndrome (NMS)-like Reactions

The development of a potentially life-threatening serotonin syndrome or Neuroleptic Malignant Syndrome (NMS)-like reactions have been reported with SNRIs and SSRIs alone, including PRISTIQ treatment, but particularly with concomitant use of serotonergic drugs (including triptans) with drugs which impair metabolism of serotonin (including MAOIs), or with antipsychotics or other dopamine antagonists. Serotonin syndrome symptoms may include mental status changes (e.g., agitation, hallucinations, coma), autonomic instability (e.g., tachycardia, labile blood pressure, hyperthermia), neuromuscular aberrations (e.g., hyperreflexia, incoordination) and/or gastrointestinal symptoms (e.g., nausea, vomiting, diarrhea). Serotonin syndrome, in its most severe form can resemble neuroleptic malignant syndrome, which includes hyperthermia, muscle rigidity, autonomic instability with possible rapid fluctuation of vital signs, and mental status changes. Patients should be monitored for the emergence of serotonin syndrome or NMS-like signs and symptoms.

The concomitant use of PRISTIQ with MAOIs intended to treat depression is contraindicated [see Contraindications (4.2)].

If concomitant treatment of PRISTIQ with a 5-hydroxytryptamine receptor agonist (triptan) is clinically warranted, careful observation of the patient is advised, particularly during treatment initiation and dose increases.

The concomitant use of PRISTIQ with serotonin precursors (such as tryptophan) is not recommended.

Treatment with PRISTIQ and any concomitant serotonergic or antidopaminergic agents, including antipsychotics, should be discontinued immediately if the above events occur and supportive symptomatic treatment should be initiated.

5.3 Elevated Blood Pressure

Patients receiving PRISTIQ should have regular monitoring of blood pressure since increases in blood pressure were observed in clinical studies. Pre-existing hypertension should be controlled before initiating treatment with PRISTIQ. Caution should be exercised in treating patients with pre-existing hypertension or other underlying conditions that might be compromised by increases in blood pressure. Cases of elevated blood pressure requiring immediate treatment have been reported with PRISTIQ.

Sustained hypertension

Sustained blood pressure increases could have adverse consequences. For patients who experience a sustained increase in blood pressure while receiving PRISTIQ, either dose reduction or discontinuation should be considered [see Adverse Reactions (6.1)]. Treatment with PRISTIQ at all doses from 50 mg/day to 400 mg/day in controlled studies was associated with sustained hypertension, defined as treatment-emergent supine diastolic blood pressure (SDBP) ≥ 90 mm Hg and ≥ 10 mm Hg above baseline for 3 consecutive on-therapy visits (see Table 2). Analyses of patients in PRISTIQ controlled studies who met criteria for sustained hypertension revealed a consistent increase in the proportion of patients who developed sustained hypertension. This was seen at all doses with a suggestion of a higher rate at 400 mg/day.

Table 2: Proportion of Patients with Sustained Elevation of Supine Diastolic Blood Pressure
Treatment Group | Proportion of Patients with Sustained Hypertension
Placebo | 0.5%
PRISTIQ 50 mg/day | 1.3%
PRISTIQ 100 mg/day | 0.7%
PRISTIQ 200 mg/day | 1.1%
PRISTIQ 400 mg/day | 2.3%

5.4 Abnormal Bleeding

SSRIs and SNRIs, including PRISTIQ, may increase the risk of bleeding events. Concomitant use of aspirin, nonsteroidal anti-inflammatory drugs, warfarin, and other anticoagulants may add to this risk. Case reports and epidemiological studies (case-control and cohort design) have demonstrated an association between use of drugs that interfere with serotonin reuptake and the occurrence of gastrointestinal bleeding. Bleeding events related to SSRIs and SNRIs have ranged from ecchymosis, hematoma, epistaxis, and petechiae to life-threatening hemorrhages. Patients should be cautioned about the risk of bleeding associated with the concomitant use of PRISTIQ and NSAIDs, aspirin, or other drugs that affect coagulation or bleeding.

5.5 Narrow-angle Glaucoma

Mydriasis has been reported in association with PRISTIQ; therefore, patients with raised intraocular pressure or those at risk of acute narrow-angle glaucoma (angle-closure glaucoma) should be monitored.

5.6 Activation of Mania/Hypomania

During all MDD and VMS (vasomotor symptoms) phase 2 and phase 3 studies, mania was reported for approximately 0.1% of patients treated with PRISTIQ. Activation of mania/hypomania has also been reported in a small proportion of patients with major affective disorder who were treated with other marketed antidepressants. As with all antidepressants, PRISTIQ should be used cautiously in patients with a history or family history of mania or hypomania.

5.7 Cardiovascular/Cerebrovascular Disease

Caution is advised in administering PRISTIQ to patients with cardiovascular, cerebrovascular, or lipid metabolism disorders [see Adverse Reactions (6.1)]. Increases in blood pressure and small increases in heart rate were observed in clinical studies with PRISTIQ. PRISTIQ has not been evaluated systematically in patients with a recent history of myocardial infarction, unstable heart disease, uncontrolled hypertension, or cerebrovascular disease. Patients with these diagnoses, except for cerebrovascular disease, were excluded from clinical studies.

5.8 Serum Cholesterol and Triglyceride Elevation

Dose-related elevations in fasting serum total cholesterol, LDL (low density lipoprotein) cholesterol, and triglycerides were observed in the controlled studies. Measurement of serum lipids should be considered during treatment with PRISTIQ [see Adverse Reactions (6.1)].

5.9 Discontinuation of Treatment with PRISTIQ

Discontinuation symptoms have been systematically and prospectively evaluated in patients treated with PRISTIQ during clinical studies in Major Depressive Disorder. Abrupt discontinuation or dose reduction has been associated with the appearance of new symptoms that include dizziness, nausea, headache, irritability, insomnia, diarrhea, anxiety, fatigue, abnormal dreams, and hyperhidrosis. In general, discontinuation events occurred more frequently with longer duration of therapy.

During marketing of SNRIs (Serotonin and Norepinephrine Reuptake Inhibitors), and SSRIs (Selective Serotonin Reuptake Inhibitors), there have been spontaneous reports of adverse events occurring upon discontinuation of these drugs, particularly when abrupt, including the following: dysphoric mood, irritability, agitation, dizziness, sensory disturbances (e.g., paresthesia, such as electric shock sensations), anxiety, confusion, headache, lethargy, emotional lability, insomnia, hypomania, tinnitus, and seizures. While these events are generally self-limiting, there have been reports of serious discontinuation symptoms.

Patients should be monitored for these symptoms when discontinuing treatment with PRISTIQ. A gradual reduction in the dose rather than abrupt cessation is recommended whenever possible. If intolerable symptoms occur following a decrease in the dose or upon discontinuation of treatment, then resuming the previously prescribed dose may be considered. Subsequently, the physician may continue decreasing the dose, but at a more gradual rate [see Dosage and Administration (2.4) and Adverse Reactions (6.1)].

5.10 Renal Impairment

In patients with moderate or severe renal impairment or end-stage renal disease (ESRD) the clearance of PRISTIQ was decreased, thus prolonging the elimination half-life of the drug. As a result, there were potentially clinically significant increases in exposures to PRISTIQ [see Clinical Pharmacology (12.6)]. Dosage adjustment (50 mg every other day) is necessary in patients with severe renal impairment or ESRD. The doses should not be escalated in patients with moderate or severe renal impairment or ESRD [see Dosage and Administration (2.2)].

5.11 Seizure

Cases of seizure have been reported in pre-marketing clinical studies with PRISTIQ. PRISTIQ has not been systematically evaluated in patients with a seizure disorder. Patients with a history of seizures were excluded from pre-marketing clinical studies. PRISTIQ should be prescribed with caution in patients with a seizure disorder.

5.12 Hyponatremia

Hyponatremia may occur as a result of treatment with SSRIs and SNRIs, including PRISTIQ. In many cases, this hyponatremia appears to be the result of the syndrome of inappropriate antidiuretic hormone secretion (SIADH). Cases with serum sodium lower than 110 mmol/L have been reported. Elderly patients may be at greater risk of developing hyponatremia with SSRIs and SNRIs. Also, patients taking diuretics or who are otherwise volume depleted can be at greater risk [see Use in Specific Populations (8.5) and Clinical Pharmacology (12.6)]. Discontinuation of PRISTIQ should be considered in patients with symptomatic hyponatremia and appropriate medical intervention should be instituted.

Signs and symptoms of hyponatremia include headache, difficulty concentrating, memory impairment, confusion, weakness, and unsteadiness, which can lead to falls. Signs and symptoms associated with more severe and/or acute cases have included hallucination, syncope, seizure, coma, respiratory arrest, and death.

5.13 Co-administration of Drugs Containing Desvenlafaxine and Venlafaxine

Desvenlafaxine is the major active metabolite of venlafaxine. Products containing desvenlafaxine and products containing venlafaxine should not be used concomitantly with PRISTIQ.

5.14 Interstitial Lung Disease and Eosinophilic Pneumonia

Interstitial lung disease and eosinophilic pneumonia associated with venlafaxine (the parent drug of PRISTIQ) therapy have been rarely reported. The possibility of these adverse events should be considered in patients treated with PRISTIQ who present with progressive dyspnea, cough, or chest discomfort. Such patients should undergo a prompt medical evaluation, and discontinuation of PRISTIQ should be considered.

6 ADVERSE REACTIONS

The following adverse reactions are discussed in greater detail in other sections of the label;

- Hypersensitivity [see Contraindications (4.1)]
- Effects on blood pressure [see Warnings and Precautions (5.3)]
- Abnormal bleeding [see Warnings and Precautions (5.4)]
- Mydriasis [see Warnings and Precautions (5.5)]
- Hypomania and mania [see Warnings and Precautions (5.6)]
- Serum cholesterol and triglyceride elevation [see Warnings and Precautions (5.8)]
- Seizure [see Warnings and Precautions (5.11)]

6.1 Clinical Studies Experience

The most commonly observed adverse reactions in PRISTIQ treated MDD patients in short-term fixed-dose studies (incidence ≥ 5% and at least twice the rate of placebo in the 50 or 100 mg dose groups) were: nausea, dizziness, insomnia, hyperhidrosis, constipation, somnolence, decreased appetite, anxiety, and specific male sexual function disorders.

Adverse reactions reported as reasons for discontinuation of treatment

Combined across 8-week placebo-controlled pre-marketing studies for major depressive disorder, 12% of the 1,834 patients who received PRISTIQ (50-400 mg) discontinued treatment due to an adverse event, compared with 3% of the 1,116 placebo-treated patients in those studies. At the recommended dose of 50 mg, the discontinuation rate due to an adverse event for PRISTIQ (4.1%) was similar to the rate for placebo (3.8%). For the 100 mg dose of PRISTIQ the discontinuation rate due to an adverse event was 8.7%.

The most common adverse reactions leading to discontinuation in at least 2% of the PRISTIQ treated patients in the short-term studies, up to 8 weeks, were: nausea (4%); dizziness, headache and vomiting (2% each); in the long-term study, up to 9 months, the most common was vomiting (2%).

Patient exposure

PRISTIQ was evaluated for safety in 3,292 patients diagnosed with major depressive disorder who participated in multiple-dose pre-marketing studies, representing 1,289 patient-years of exposure. Among these 3,292 PRISTIQ treated patients, 1,834 patients were exposed to PRISTIQ in 8-week, placebo-controlled studies at doses ranging from 50 to 400 mg/day. Out of the 1,834 patients, 687 PRISTIQ treated patients continued into a 10-month open-label study. Of the total 3,292 patients exposed to at least one dose of PRISTIQ, 1,070 were exposed to PRISTIQ for 6 months, representing 842 patient-years of exposure, and 274 were exposed for one year, representing 241 patient-years of exposure.

Because clinical studies are conducted under widely varying conditions, adverse reaction rates observed in the clinical studies of a drug cannot be directly compared to rates in the clinical studies of another drug and may not reflect the rates observed in practice.

Common adverse reactions in placebo-controlled MDD studies

Table 3 shows the incidence of common adverse reactions that occurred in ≥ 2% of PRISTIQ treated MDD patients at any dose in the 8-week, placebo-controlled, fixed dose, pre-marketing clinical studies. In general, the adverse reactions were most frequent in the first week of treatment.

Table 3: Common Adverse Reactions: Percentage of Patients (≥ 2% in any Fixed-Dose Group) in MDD 8‑Week Placebo-Controlled Studiesa
 | Percentage of Patients Reporting Reaction
 |  | PRISTIQ
System Organ Class Preferred Term | Placebo | 50 mg | 100 mg | 200 mg | 400 mg
Cardiac disorders
Palpitations | 2 | 1 | 3 | 2 | 3
Tachycardia | 1 | 1 | <1 | 1 | 2
Blood pressure increased | 1 | 1 | 1 | 2 | 2
Gastrointestinal disorders
Nausea | 10 | 22 | 26 | 36 | 41
Dry mouth | 9 | 11 | 17 | 21 | 25
Diarrhea | 9 | 11 | 9 | 7 | 5
Constipation | 4 | 9 | 9 | 10 | 14
Vomiting | 3 | 3 | 4 | 6 | 9
General disorders and administration site conditions
Fatigue | 4 | 7 | 7 | 10 | 11
Chills | 1 | 1 | <1 | 3 | 4
Feeling jittery | 1 | 1 | 2 | 3 | 3
Asthenia | 1 | 1 | 2 | 1 | 1
Metabolism and nutrition disorders
Decreased appetite | 2 | 5 | 8 | 10 | 10
Weight decreased | 1 | 2 | 1 | 1 | 2
Nervous system disorders
Dizziness | 5 | 13 | 10 | 15 | 16
Somnolence | 4 | 4 | 9 | 12 | 12
Headache | 23 | 20 | 22 | 29 | 25
Tremor | 2 | 2 | 3 | 9 | 9
Paraesthesia | 1 | 2 | 2 | 1 | 3
Disturbance in attention | <1 | <1 | 1 | 2 | 1
Psychiatric disorders
Insomnia | 6 | 9 | 12 | 14 | 15
Anxiety | 2 | 3 | 5 | 4 | 4
Nervousness | 1 | <1 | 1 | 2 | 2
Irritability | 1 | 2 | 2 | 2 | 2
Abnormal dreams | 1 | 2 | 3 | 2 | 4
Renal and urinary disorders
Urinary hesitation | 0 | <1 | 1 | 2 | 2
Respiratory, thoracic and mediastinal disorders
Yawning | <1 | 1 | 1 | 4 | 3
Skin and subcutaneous tissue disorders
Hyperhidrosis | 4 | 10 | 11 | 18 | 21
Rash | <1 | 1 | 1 | 2 | <1
Special Senses
Vision blurred | 1 | 3 | 4 | 4 | 4
Mydriasis | <1 | 2 | 2 | 6 | 6
Vertigo | 1 | 2 | 1 | 5 | 3
Tinnitus | 1 | 2 | 1 | 1 | 2
Dysgeusia | 1 | 1 | 1 | 1 | 2
Vascular disorders
Hot flush | <1 | 1 | 1 | 2 | 2
a: Percentage based on the number of patients (placebo, n = 636; PRISTIQ 50 mg, n = 317; PRISTIQ 100 mg, n = 424; PRISTIQ 200 mg, n = 307; PRISTIQ 400 mg, n = 317).

Sexual function adverse reactions

Table 4 shows the incidence of sexual function adverse reactions that occurred in ≥ 2% of PRISTIQ treated MDD patients in any fixed-dose group (8-week, placebo-controlled, fixed and flexible-dose, pre-marketing clinical studies).

Table 4: Sexual Function Disorders: Adverse Reactions (≥ 2% in Mena or Womenb in any PRISTIQ Group) During the On-Therapy Period
 |  | PRISTIQ
System Organ Class Preferred Term | Placebo | 50 mg | 100 mg | 200 mg | 400 mg
Men only
Anorgasmia | 0 | 0 | 3 | 5 | 8
Libido decreased | 1 | 4 | 5 | 6 | 3
Orgasm abnormal | 0 | 0 | 1 | 2 | 3
Ejaculation delayed | <1 | 1 | 5 | 7 | 6
Erectile dysfunction | 1 | 3 | 6 | 8 | 11
Ejaculation disorder | 0 | 0 | 1 | 2 | 5
Ejaculation failure | 0 | 1 | 0 | 2 | 2
Sexual dysfunction | 0 | 1 | 0 | 0 | 2
Women only
Anorgasmia | 0 | 1 | 1 | 0 | 3
a: Percentage based on the number of men (placebo, n = 239; PRISTIQ 50 mg, n = 108; PRISTIQ 100 mg, n = 157; PRISTIQ 200 mg, n = 131; PRISTIQ 400 mg, n = 154).
b: Percentage based on the number of women (placebo, n = 397; PRISTIQ 50 mg, n = 209; PRISTIQ 100 mg, n = 267; PRISTIQ 200 mg, n = 176; PRISTIQ 400 mg, n = 163).

Other adverse reactions observed in pre-marketing clinical studies

Other infrequent adverse reactions, not described elsewhere in section 6.1, occurring at an incidence of < 2% in MDD patients treated with PRISTIQ were:

Immune system disorders – Hypersensitivity.

Investigations – Weight increased, liver function test abnormal, blood prolactin increased.

Nervous system disorders – Convulsion, syncope, extrapyramidal disorder.

Musculoskeletal and connective tissue disorders – Musculoskeletal stiffness.

Psychiatric disorders – Depersonalization, hypomania, bruxism.

Respiratory, thoracic and mediastinal disorders – Epistaxis.

Vascular disorders – Orthostatic hypotension.

In clinical studies, there were uncommon reports of ischemic cardiac adverse events, including myocardial ischemia, myocardial infarction, and coronary occlusion requiring revascularization; these patients had multiple underlying cardiac risk factors. More patients experienced these events during PRISTIQ treatment as compared to placebo [see Warnings and Precautions (5.7)].

Discontinuation events

Adverse events reported in association with abrupt discontinuation, dose reduction or tapering of treatment in MDD clinical studies at a rate of ≥ 5% include: dizziness, nausea, headache, irritability, insomnia, diarrhea, anxiety, abnormal dreams, fatigue, and hyperhidrosis. In general, discontinuation events occurred more frequently with longer duration of therapy [see Dosage and Administration (2.4) and Warnings and Precautions (5.9)].

Laboratory, ECG and vital sign changes observed in MDD clinical studies

The following changes were observed in placebo-controlled, short-term, pre-marketing MDD studies with PRISTIQ.

Lipids

Elevations in fasting serum total cholesterol, LDL (low density lipoproteins) cholesterol, and triglycerides occurred in the controlled studies. Some of these abnormalities were considered potentially clinically significant [see Warnings and Precautions (5.8)].

The percentage of patients who exceeded a predetermined threshold value is shown in Table 5.

Table 5: Incidence (%) of Patients With Lipid Abnormalities of Potential Clinical Significance*
 |  | PRISTIQ
 | Placebo | 50 mg | 100 mg | 200 mg | 400 mg
Total Cholesterol *(Increase of ≥ 50 mg/dl and an absolute value of ≥ 261 mg/dl) | 2 | 3 | 4 | 4 | 10
LDL Cholesterol *(Increase ≥ 50 mg/dl and an absolute value of ≥ 190 mg/dl) | 0 | 1 | 0 | 1 | 2
Triglycerides, fasting *(Fasting: ≥ 327 mg/dl) | 3 | 2 | 1 | 4 | 6

Proteinuria

Proteinuria, greater than or equal to trace, was observed in the fixed-dose controlled studies (see Table 6). This proteinuria was not associated with increases in BUN or creatinine and was generally transient.

Table 6: Incidence (%) of Patients with Proteinuria in the Fixed-dose Clinical Studies
 |  | PRISTIQ
 | Placebo | 50 mg | 100 mg | 200 mg | 400 mg
Proteinuria | 4 | 6 | 8 | 5 | 7

ECG changes

Electrocardiograms were obtained from 1,492 PRISTIQ treated patients with major depressive disorder and 984 placebo-treated patients in clinical studies lasting up to 8 weeks. No clinically relevant differences were observed between PRISTIQ treated and placebo-treated patients for QT, QTc, PR, and QRS intervals. In a thorough QTc study with prospectively determined criteria, desvenlafaxine did not cause QT prolongation. No difference was observed between placebo and desvenlafaxine treatments for the QRS interval.

Vital sign changes

Table 7 summarizes the changes that were observed in placebo-controlled, short-term, pre-marketing studies with PRISTIQ in patients with MDD (doses 50 to 400 mg).

Table 7: Mean Changes in Vital Signs at Final on Therapy for All Short-term, Fixed-dose Controlled Studies
 |  | PRISTIQ
 | Placebo | 50 mg | 100 mg | 200 mg | 400 mg
Blood pressure
Supine systolic bp (mm Hg) | -1.4 | 1.2 | 2.0 | 2.5 | 2.1
Supine diastolic bp (mm Hg) | -0.6 | 0.7 | 0.8 | 1.8 | 2.3
Pulse rate
Supine pulse (bpm) | -0.3 | 1.3 | 1.3 | 0.9 | 4.1
Weight (kg) | 0.0 | -0.4 | -0.6 | -0.9 | -1.1

At the final on-therapy assessment in the 6-month, double-blind, placebo-controlled phase of a long-term study in patients who had responded to PRISTIQ during the initial 12-week, open-label phase, there was no statistical difference in mean weight change between PRISTIQ and placebo-treated patients.

Orthostatic hypotension

In the short-term, placebo-controlled clinical studies with doses of 50-400 mg, systolic orthostatic hypotension (decrease ≥ 30 mm Hg from supine to standing position) occurred more frequently in patients ≥ 65 years of age receiving PRISTIQ (8.0%, 7/87) versus placebo (2.5%, 1/40), compared to patients < 65 years of age receiving PRISTIQ (0.9%, 18/1,937) versus placebo (0.7%, 8/1,218).

6.2 Adverse Reactions Identified During Post-Approval Use

The following adverse reaction has been identified during post-approval use of PRISTIQ. Because post-approval reactions are reported voluntarily from a population of uncertain size, it is not always possible to reliably estimate their frequency or establish a causal relationship to drug exposure:

Skin and subcutaneous tissue disorders – Angioedema.

6.3 Adverse Reactions Reported With Other SNRIs

Although the following are not considered adverse reactions for PRISTIQ, they are adverse reactions for other SNRIs and may also occur with PRISTIQ: gastrointestinal bleeding, hallucinations, photosensitivity reactions and severe cutaneous reactions (such as Stevens-Johnson Syndrome, toxic epidermal necrolysis, and/or erythema multiforme).

7 DRUG INTERACTIONS

7.1 Central Nervous System (CNS)-Active Agents

The risk of using PRISTIQ in combination with other CNS-active drugs has not been systematically evaluated. Consequently, caution is advised when PRISTIQ is taken in combination with other CNS-active drugs [see Warnings and Precautions (5.13)].

7.2 Monoamine Oxidase Inhibitors (MAOI)

Adverse reactions, some of which were serious, have been reported in patients who have recently been discontinued from a monoamine oxidase inhibitor (MAOI) and started on antidepressants with pharmacological properties similar to PRISTIQ (SNRIs or SSRIs), or who have recently had SNRI or SSRI therapy discontinued prior to initiation of an MAOI [see Contraindications (4.2)].

7.3 Serotonergic Drugs

Based on the mechanism of action of PRISTIQ and the potential for serotonin syndrome, caution is advised when PRISTIQ is co-administered with other drugs that may affect the serotonergic neurotransmitter systems [see Warnings and Precautions (5.2)].

7.4 Drugs that Interfere with Hemostasis (e.g., NSAIDs, Aspirin, and Warfarin)

Serotonin release by platelets plays an important role in hemostasis. Epidemiological studies of case-control and cohort design that have demonstrated an association between use of psychotropic drugs that interfere with serotonin reuptake and the occurrence of upper gastrointestinal bleeding. These studies have also shown that concurrent use of an NSAID or aspirin may potentiate this risk of bleeding. Altered anticoagulant effects, including increased bleeding, have been reported when SSRIs and SNRIs are coadministered with warfarin. Patients receiving warfarin therapy should be carefully monitored when PRISTIQ is initiated or discontinued.

7.5 Ethanol

A clinical study has shown that desvenlafaxine does not increase the impairment of mental and motor skills caused by ethanol. However, as with all CNS-active drugs, patients should be advised to avoid alcohol consumption while taking PRISTIQ.

7.6 Potential for Other Drugs to Affect Desvenlafaxine

Inhibitors of CYP3A4 (ketoconazole)

CYP3A4 is a minor pathway for the metabolism of PRISTIQ. In a clinical study, ketoconazole (200 mg BID) increased the area under the concentration vs. time curve (AUC) of PRISTIQ (400 mg single dose) by about 43% and Cmax by about 8%. Concomitant use of PRISTIQ with potent inhibitors of CYP3A4 may result in higher concentrations of PRISTIQ.

Inhibitors of other CYP enzymes

Based on in vitro data, drugs that inhibit CYP isozymes 1A1, 1A2, 2A6, 2D6, 2C8, 2C9, 2C19, and 2E1 are not expected to have significant impact on the pharmacokinetic profile of PRISTIQ.

7.7 Potential for Desvenlafaxine to Affect Other Drugs

Drugs metabolized by CYP2D6 (desipramine)

In vitro studies showed minimal inhibitory effect of desvenlafaxine on CYP2D6.

Clinical studies have shown that desvenlafaxine does not have a clinically relevant effect on CYP2D6 metabolism at the dose of 100 mg daily. When desvenlafaxine succinate was administered at a dose of 100 mg daily in conjunction with a single 50 mg dose of desipramine, a CYP2D6 substrate, the Cmax and AUC of desipramine increased approximately 25% and 17%, respectively. When 400 mg (8 times the recommended 50 mg dose) was administered, the Cmax and AUC of desipramine increased approximately 50% and 90%, respectively. Concomitant use of desvenlafaxine with a drug metabolized by CYP2D6 can result in higher concentrations of that drug.

Drugs metabolized by CYP3A4 (midazolam)

In vitro, desvenlafaxine does not inhibit or induce the CYP3A4 isozyme.

In a clinical study, PRISTIQ 400 mg daily (8 times the recommended 50 mg dose) was co‑administered with a single 4 mg dose of midazolam (a CYP3A4 substrate). The AUC and Cmax of midazolam decreased by approximately 31% and 16%, respectively. Concomitant use of PRISTIQ with a drug metabolized by CYP3A4 can result in lower exposures to that drug.

Drugs metabolized by CYP1A2, 2A6, 2C8, 2C9 and 2C19

In vitro, desvenlafaxine does not inhibit CYP1A2, 2A6, 2C8, 2C9, and 2C19 isozymes and would not be expected to affect the pharmacokinetics of drugs that are metabolized by these CYP isozymes.

7.8 P-glycoprotein Transporter

In vitro, desvenlafaxine is not a substrate or an inhibitor for the P-glycoprotein transporter.

The pharmacokinetics of PRISTIQ are unlikely to be affected by drugs that inhibit the P‑glycoprotein transporter, and desvenlafaxine is not likely to affect the pharmacokinetics of drugs that are substrates of the P-glycoprotein transporter.

7.9 Electroconvulsive Therapy

There are no clinical data establishing the risks and/or benefits of electroconvulsive therapy combined with PRISTIQ treatment.

7.10 Drug-Laboratory Test Interactions

False-positive urine immunoassay screening tests for phencyclidine (PCP) and amphetamine have been reported in patients taking desvenlafaxine. This is due to lack of specificity of the screening tests. False positive test results may be expected for several days following discontinuation of desvenlafaxine therapy. Confirmatory tests, such as gas chromatography/mass spectrometry, will distinguish desvenlafaxine from PCP and amphetamine.

8 USE IN SPECIFIC POPULATIONS

8.1 Pregnancy

Patients should be advised to notify their physician if they become pregnant or intend to become pregnant during therapy.

Teratogenic effects – Pregnancy Category C

When desvenlafaxine succinate was administered orally to pregnant rats and rabbits during the period of organogenesis, there was no evidence of teratogenicity in rats at any doses tested, up to 10 times a human dose of 100 mg/day (on a mg/m^2 basis) in rats, and up to 15 times a human dose of 100 mg/day (on a mg/m^2 basis) in rabbits. However, fetal weights were decreased in rats, with a no-effect dose 10 times a human dose of 100 mg/day (on a mg/m^2 basis).

When desvenlafaxine succinate was administered orally to pregnant rats throughout gestation and lactation, there was a decrease in pup weights and an increase in pup deaths during the first four days of lactation. The cause of these deaths is not known. The no-effect dose for rat pup mortality was 10 times a human dose of 100 mg/day (on a mg/m^2 basis). Post-weaning growth and reproductive performance of the progeny were not affected by maternal treatment with desvenlafaxine at a dose 29 times a human dose of 100 mg/day (on a mg/m^2 basis).

There are no adequate and well-controlled studies of PRISTIQ in pregnant women. Therefore, PRISTIQ should be used during pregnancy only if the potential benefits justify the potential risks.

Non-teratogenic effects

Neonates exposed to SNRIs (Serotonin and Norepinephrine Reuptake Inhibitors), or SSRIs (Selective Serotonin Reuptake Inhibitors), late in the third trimester have developed complications requiring prolonged hospitalization, respiratory support, and tube feeding. Such complications can arise immediately upon delivery. Reported clinical findings have included respiratory distress, cyanosis, apnea, seizures, temperature instability, feeding difficulty, vomiting, hypoglycemia, hypotonia, hypertonia, hyperreflexia, tremor, jitteriness, irritability, and constant crying. These features are consistent with either a direct toxic effect of SSRIs and SNRIs or, possibly, a drug discontinuation syndrome. It should be noted that, in some cases, the clinical picture is consistent with serotonin syndrome [see Warnings and Precautions (5.2)]. When treating a pregnant woman with PRISTIQ during the third trimester, the physician should carefully consider the potential risks and benefits of treatment [see Dosage and Administration (2.2)].

8.2 Labor and Delivery

The effect of PRISTIQ on labor and delivery in humans is unknown. PRISTIQ should be used during labor and delivery only if the potential benefits justify the potential risks.

8.3 Nursing Mothers

Desvenlafaxine (O-desmethylvenlafaxine) is excreted in human milk. Because of the potential for serious adverse reactions in nursing infants from PRISTIQ, a decision should be made whether or not to discontinue nursing or to discontinue the drug, taking into account the importance of the drug to the mother. Only administer PRISTIQ to breastfeeding women if the expected benefits outweigh any possible risk.

8.4 Pediatric Use

Safety and effectiveness in the pediatric population have not been established [see Box Warning and Warnings and Precautions (5.1)]. Anyone considering the use of PRISTIQ in a child or adolescent must balance the potential risks with the clinical need.

8.5 Geriatric Use

Of the 3,292 patients in clinical studies with PRISTIQ, 5% were 65 years of age or older. No overall differences in safety or efficacy were observed between these patients and younger patients; however, in the short-term, placebo-controlled studies, there was a higher incidence of systolic orthostatic hypotension in patients ≥ 65 years of age compared to patients < 65 years of age treated with PRISTIQ [see Adverse Reactions (6) ]. For elderly patients, possible reduced renal clearance of desvenlafaxine should be considered when determining dose [see Dosage and Administration (2.2) and Clinical Pharmacology (12.6)]. If PRISTIQ is poorly tolerated, every other day dosing can be considered.

SSRIs and SNRIs, including PRISTIQ, have been associated with cases of clinically significant hyponatremia in elderly patients, who may be at greater risk for this adverse event [see Warnings and Precautions (5.12)].

Greater sensitivity of some older individuals cannot be ruled out.

8.6 Renal Impairment

In subjects with renal impairment the clearance of PRISTIQ was decreased. In subjects with severe renal impairment (24-hr CrCl < 30 mL/min) and end-stage renal disease, elimination half-lives were significantly prolonged, increasing exposures to PRISTIQ; therefore, dosage adjustment is recommended in these patients [see Dosage and Administration (2.2) and Clinical Pharmacology (12.6)].

8.7 Hepatic Impairment

The mean t1/2 changed from approximately 10 hours in healthy subjects and subjects with mild hepatic impairment to 13 and 14 hours in moderate and severe hepatic impairment, respectively. The recommended dose in patients with hepatic impairment is 50 mg/day. Dose escalation above 100 mg/day is not recommended [see Clinical Pharmacology (12.6)].

9 DRUG ABUSE AND DEPENDENCE

9.1 Controlled Substance

Desvenlafaxine is not a controlled substance.

9.2 Abuse and Dependence

Although PRISTIQ has not been systematically studied in preclinical or clinical studies for its potential for abuse, no indication of drug-seeking behavior was seen in the clinical studies. However, it is not possible to predict on the basis of pre-marketing experience, the extent to which a CNS-active drug will be misused, diverted, and/or abused once marketed. Consequently, physicians should carefully evaluate patients for a history of drug abuse and follow such patients closely, observing them for signs of misuse or abuse of PRISTIQ (e.g., development of tolerance, incrementation of dose, drug-seeking behavior).

10 OVERDOSAGE

10.1 Human Experience with Overdosage

There is limited clinical experience with desvenlafaxine succinate overdosage in humans. In pre-marketing clinical studies, no cases of fatal acute overdose of desvenlafaxine were reported.

Among the patients included in the MDD pre-marketing studies of PRISTIQ, there were four adults who ingested desvenlafaxine succinate (4000 mg [desvenlafaxine alone], 900, 1800 and 5200 mg [in combination with other drugs]); all patients recovered. In addition, one patient's 11-month-old child accidentally ingested 600 mg of desvenlafaxine succinate, was treated, and recovered. The adverse reactions reported within 5 days of an overdose > 600 mg that were possibly related to PRISTIQ included: headache, vomiting, agitation, dizziness, nausea, constipation, diarrhea, dry mouth, paresthesia, and tachycardia.

Desvenlafaxine (PRISTIQ) is the major active metabolite of venlafaxine. Overdose experience reported with venlafaxine (the parent drug of PRISTIQ) is presented below; the identical information can be found in the Overdosage section of the venlafaxine package insert.

In postmarketing experience, overdose with venlafaxine (the parent drug of PRISTIQ) has occurred predominantly in combination with alcohol and/or other drugs. The most commonly reported events in overdosage include tachycardia, changes in level of consciousness (ranging from somnolence to coma), mydriasis, seizures, and vomiting. Electrocardiogram changes (e.g., prolongation of QT interval, bundle branch block, QRS prolongation), sinus and ventricular tachycardia, bradycardia, hypotension, rhabdomyolysis, vertigo, liver necrosis, serotonin syndrome, and death have been reported.

Published retrospective studies report that venlafaxine overdosage may be associated with an increased risk of fatal outcomes compared to that observed with SSRI antidepressant products, but lower than that for tricyclic antidepressants. Epidemiological studies have shown that venlafaxine-treated patients have a higher pre-existing burden of suicide risk factors than SSRI-treated patients. The extent to which the finding of an increased risk of fatal outcomes can be attributed to the toxicity of venlafaxine in overdosage, as opposed to some characteristic(s) of venlafaxine-treated patients, is not clear.

Prescriptions for PRISTIQ should be written for the smallest quantity of tablets consistent with good patient management, in order to reduce the risk of overdose.

10.2 Management of Overdosage

Treatment should consist of those general measures employed in the management of overdosage with any SSRI/SNRI.

Ensure an adequate airway, oxygenation, and ventilation. Monitor cardiac rhythm and vital signs. General supportive and symptomatic measures are also recommended. Gastric lavage with a large-bore orogastric tube with appropriate airway protection, if needed, may be indicated if performed soon after ingestion or in symptomatic patients. Activated charcoal should be administered.

Induction of emesis is not recommended. Because of the moderate volume of distribution of this drug, forced diuresis, dialysis, hemoperfusion, and exchange transfusion are unlikely to be of benefit. No specific antidotes for desvenlafaxine are known.

In managing an overdose, consider the possibility of multiple drug involvement. The physician should consider contacting a poison control center for additional information on the treatment of any overdose. Telephone numbers for certified poison control centers are listed in the Physicians Desk Reference® (PDR).

11 DESCRIPTION

PRISTIQ is an extended-release tablet for oral administration that contains desvenlafaxine succinate, a structurally novel SNRI for the treatment of MDD. Desvenlafaxine (O‑desmethylvenlafaxine) is the major active metabolite of the antidepressant venlafaxine, a medication used to treat major depressive, generalized anxiety, social anxiety and panic disorders.

Desvenlafaxine is designated RS-4-[2-dimethylamino-1-(1-hydroxycyclohexyl)ethyl]phenol and has the empirical formula of C16H25NO2 (free base) and C16H25NO2•C4H6O4•H2O (succinate monohydrate). Desvenlafaxine succinate monohydrate has a molecular weight of 399.48. The structural formula is shown below.

Desvenlafaxine succinate is a white to off-white powder that is soluble in water. The solubility of desvenlafaxine succinate is pH dependent. Its octanol:aqueous system (at pH 7.0) partition coefficient is 0.21.

PRISTIQ is formulated as an extended-release tablet for once-a-day oral administration.

Each tablet contains 76 or 152 mg of desvenlafaxine succinate equivalent to 50 or 100 mg of desvenlafaxine, respectively.

Inactive ingredients for the 50 mg tablet consist of hypromellose, microcrystalline cellulose, talc, magnesium stearate and film coating, which consists of polyvinyl alcohol, polyethylene glycol, talc, titanium dioxide, and iron oxides.

Inactive ingredients for the 100 mg tablet consist of hypromellose, microcrystalline cellulose, talc, magnesium stearate and film coating, which consists of polyvinyl alcohol, polyethylene glycol, talc, titanium dioxide, iron oxide and FD&C yellow #6.

12 CLINICAL PHARMACOLOGY

12.1 Mechanism of Action

Non-clinical studies have shown that desvenlafaxine succinate is a potent and selective serotonin and norepinephrine reuptake inhibitor (SNRI). The clinical efficacy of desvenlafaxine succinate is thought to be related to the potentiation of these neurotransmitters in the central nervous system.

12.2 Pharmacodynamics

Desvenlafaxine lacked significant affinity for numerous receptors, including muscarinic-cholinergic, H1-histaminergic, or α1-adrenergic receptors in vitro. PRISTIQ also lacked monoamine oxidase (MAO) inhibitory activity.

12.3 Pharmacokinetics

The single-dose pharmacokinetics of desvenlafaxine are linear and dose-proportional in a dose range of 100 to 600 mg/day. The mean terminal half-life, t1/2, is approximately 11 hours. With once-daily dosing, steady-state plasma concentrations are achieved within approximately 4-5 days. At steady-state, multiple-dose accumulation of desvenlafaxine is linear and predictable from the single-dose pharmacokinetic profile.

12.4 Absorption and Distribution

The absolute oral bioavailability of PRISTIQ after oral administration is about 80%. Mean time to peak plasma concentrations (Tmax) is about 7.5 hours after oral administration.

A food-effect study involving administration of PRISTIQ to healthy subjects under fasting and fed conditions (high-fat meal) indicated that the Cmax was increased about 16% in the fed state, while the AUCs were similar. This difference is not clinically significant; therefore, PRISTIQ can be taken without regard to meals [see Dosage and Administration (2.1)].

The plasma protein binding of desvenlafaxine is low (30%) and is independent of drug concentration. The desvenlafaxine volume of distribution at steady-state following intravenous administration is 3.4 L/kg, indicating distribution into nonvascular compartments.

12.5 Metabolism and Elimination

Desvenlafaxine is primarily metabolized by conjugation (mediated by UGT isoforms) and, to a minor extent, through oxidative metabolism. CYP3A4 is the cytochrome P450 isozyme mediating the oxidative metabolism (N-demethylation) of desvenlafaxine. The CYP2D6 metabolic pathway is not involved, and after administration of 100 mg, the pharmacokinetics of desvenlafaxine was similar in subjects with CYP2D6 poor and extensive metabolizer phenotype. Approximately 45% of desvenlafaxine is excreted unchanged in urine at 72 hours after oral administration. Approximately 19% of the administered dose is excreted as the glucuronide metabolite and < 5% as the oxidative metabolite (N,O-didesmethylvenlafaxine) in urine.

12.6 Special Populations

Age

In a study of healthy subjects administered doses of up to 300 mg, there was an approximate 32% increase in Cmax and a 55% increase in AUC in subjects older than 75 years of age (n = 17), compared with subjects 18 to 45 years of age (n = 16). Subjects 65 to 75 years of age (n = 15) had no change in Cmax, but an approximately 32% increase in AUC, compared to subjects 18 to 45 years of age [see Dosage and Administration (2.2)].

Gender

In a study of healthy subjects administered doses of up to 300 mg, women had an approximately 25% higher Cmax and an approximately 10% higher AUC than age-matched men. No adjustment of dosage on the basis of gender is needed.

Race

Pharmacokinetic analysis showed that race (White, n = 466; Black, n = 97; Hispanic, n = 39; Other, n = 33) had no apparent effect on the pharmacokinetics of PRISTIQ. No adjustment of dosage on the basis of race is needed.

Hepatic insufficiency

The disposition of desvenlafaxine succinate after administration of 100 mg was studied in subjects with mild (Child-Pugh A, n = 8), moderate (Child-Pugh B, n = 8), and severe (Child-Pugh C, n = 8) hepatic impairment and to healthy subjects (n = 12).

Average AUC was increased by approximately 31% and 35% in patients with moderate and severe hepatic impairment, respectively, as compared to healthy subjects. Average AUC values were similar in subjects with mild hepatic impairment and healthy subjects (< 5% difference).

Systemic clearance (CL/F) was decreased by approximately 20% and 36% in patients with moderate and severe hepatic impairment, respectively, as compared to healthy subjects. CL/F values were comparable in mild hepatic impairment and healthy subjects (< 5% difference).

The mean t1/2 changed from approximately 10 hours in healthy subjects and subjects with mild hepatic impairment to 13 and 14 hours in moderate and severe hepatic impairment, respectively. The recommended dose in patients with hepatic impairment is 50 mg/day. Dose escalation above 100 mg/day is not recommended [see Use in Specific Populations (8.7)].

Renal insufficiency

The disposition of desvenlafaxine after administration of 100 mg was studied in subjects with mild (n = 9), moderate (n = 8), severe (n = 7) and end-stage renal disease [ESRD] (n = 9) requiring dialysis and in healthy, age-matched control subjects (n = 8). Elimination was significantly correlated with creatinine clearance. Increases in AUCs of about 42% in mild renal impairment (24‑hr CrCl = 50‑80 mL/min), about 56% in moderate renal impairment (24‑hr CrCl = 30‑50 mL/min), about 108% in severe renal impairment (24‑hr CrCl ≤ 30 mL/min), and about 116% in ESRD subjects were observed, compared with healthy, age-matched control subjects.

The mean terminal half-life (t1/2) was prolonged from 11.1 hours in the control subjects to approximately 13.5, 15.5, 17.6, and 22.8 hours in mild, moderate, severe renal impairment and ESRD subjects, respectively. Less than 5% of the drug in the body was cleared during a standard 4-hour hemodialysis procedure.

The recommended dose in patients with moderate renal impairment is 50 mg per day. Dosage adjustment (50 mg every other day) is recommended in patients with severe renal impairment or ESRD. Doses should not be escalated in patients with moderate or severe renal impairment, or ESRD [see Dosage and Administration (2.2) and Use in Specific Populations (8.6)].

13 NONCLINICAL TOXICOLOGY

13.1 Carcinogenesis, Mutagenesis, Impairment of Fertility

Carcinogenesis

Desvenlafaxine succinate administered by oral gavage to mice and rats for 2 years did not increase the incidence of tumors in either study.

Mice received desvenlafaxine succinate at dosages up to 500/300 mg/kg/day (dosage lowered after 45 weeks of dosing). The 300 mg/kg/day dose is 15 times a human dose of 100 mg/day on a mg/m^2 basis.

Rats received desvenlafaxine succinate at dosages up to 300 mg/kg/day (males) or 500 mg/kg/day (females). The highest dose is 29 (males) or 48 (females) times a human dose of 100 mg/day on a mg/m^2 basis.

Mutagenesis

Desvenlafaxine was not mutagenic in the in vitro bacterial mutation assay (Ames test) and was not clastogenic in an in vitro chromosome aberration assay in cultured CHO cells, an in vivo mouse micronucleus assay, or an in vivo chromosome aberration assay in rats. Additionally, desvenlafaxine was not genotoxic in the in vitro CHO mammalian cell forward mutation assay and was negative in the in vitro BALB/c-3T3 mouse embryo cell transformation assay.

Impairment of fertility

Reduced fertility was observed in a study in which both male and female rats received desvenlafaxine succinate. This effect was noted at oral doses approximately 10 times a human dose of 100 mg/day on a mg/m^2 basis. There was no effect on fertility at oral doses approximately 3 times a human dose of 100 mg/day on a mg/m^2 basis.

14 CLINICAL STUDIES

The efficacy of PRISTIQ as a treatment for depression was established in four 8-week, randomized, double-blind, placebo-controlled, fixed-dose studies (at doses of 50 mg/day to 400 mg/day) in adult outpatients who met the Diagnostic and Statistical Manual of Mental Disorders (DSM-IV) criteria for major depressive disorder. In the first study, patients received 100 mg (n = 114), 200 mg (n = 116), or 400 mg (n = 113) of PRISTIQ once daily, or placebo (n = 118). In a second study, patients received either 200 mg (n = 121) or 400 mg (n = 124) of PRISTIQ once daily, or placebo (n = 124). In two additional studies, patients received 50 mg (n = 150 and n = 164) or 100 mg (n = 147 and n = 158) of PRISTIQ once daily, or placebo (n = 150 and n = 161).

PRISTIQ showed superiority over placebo as measured by improvement in the 17-item Hamilton Rating Scale for Depression (HAM-D17) total score in four studies and overall improvement, as measured by the Clinical Global Impressions Scale - Improvement (CGI-I), in three of the four studies. In studies directly comparing 50 mg/day and 100 mg/day there was no suggestion of a greater effect with the higher dose and adverse events and discontinuations were more frequent at higher doses [see Dosage and Administration (2.1)].

Analyses of the relationships between treatment outcome and age and treatment outcome and gender did not suggest any differential responsiveness on the basis of these patient characteristics. There was insufficient information to determine the effect of race on outcome in these studies.

16 HOW SUPPLIED/STORAGE AND HANDLING

PRISTIQ® (desvenlafaxine) Extended-Release Tablets are available as follows:

50 mg, light pink, square pyramid tablet debossed with “W” (over) “50” on the flat side

NDC 54868-2932-0, bottle of 30 tablets in unit-of-use package

Store at 20° to 25°C (68° to 77°F); excursions permitted to 15° to 30°C (59° to 86°F) [see USP Controlled Room Temperature].

Each tablet contains 76 or 152 mg of desvenlafaxine succinate equivalent to 50 or 100 mg of desvenlafaxine, respectively.

The unit-of-use package is intended to be dispensed as a unit.

The appearance of these tablets is a trademark of Wyeth Pharmaceuticals.

17 PATIENT COUNSELING INFORMATION

Advise patients, their families, and their caregivers about the benefits and risks associated with treatment with PRISTIQ and counsel them in its appropriate use.

Advise patients, their families, and their caregivers to read the Medication Guide and assist them in understanding its contents. The complete text of the Medication Guide is reprinted at the end of this document.

17.1 Suicide Risk

Advise patients, their families and caregivers to look for the emergence of suicidality, especially early during treatment and when the dose is adjusted up or down [see Box Warning and Warnings and Precautions (5.1)].

17.2 Concomitant Medication

Advise patients taking PRISTIQ not to use concomitantly other products containing desvenlafaxine or venlafaxine. Healthcare professionals should instruct patients not to take PRISTIQ with an MAOI or within 14 days of stopping an MAOI and to allow 7 days after stopping PRISTIQ before starting an MAOI [see Contraindications (4.2)].

17.3 Serotonin Syndrome or Neuroleptic Malignant Syndrome (NMS)-like Reactions

Caution patients about the risk of serotonin syndrome or Neuroleptic Malignant Syndrome (NMS)-like reactions, particularly with the concomitant use of PRISTIQ and triptans, tramadol, tryptophan supplements, other serotonergic agents, or antipsychotic drugs [see Warnings and Precautions (5.2) and Drug Interactions (7.3)].

17.4 Elevated Blood Pressure

Advise patients that they should have regular monitoring of blood pressure when taking PRISTIQ [see Warnings and Precautions (5.3)].

17.5 Abnormal Bleeding

Patients should be cautioned about the concomitant use of PRISTIQ and NSAIDs, aspirin, warfarin, or other drugs that affect coagulation since combined use of psychotropic drugs that interfere with serotonin reuptake and these agents has been associated with an increased risk of bleeding [see Warnings and Precautions (5.4)].

17.6 Narrow-angle Glaucoma

Advise patients with raised intraocular pressure or those at risk of acute narrow-angle glaucoma (angle-closure glaucoma) that mydriasis has been reported and they should be monitored [see Warnings and Precautions (5.5)].

17.7 Activation of Mania/Hypomania

Advise patients, their families and caregivers to observe for signs of activation of mania/hypomania [see Warnings and Precautions (5.6)].

17.8 Cardiovascular/Cerebrovascular Disease

Caution is advised in administering PRISTIQ to patients with cardiovascular, cerebrovascular, or lipid metabolism disorders [see Adverse Reactions (6.1) and Warnings and Precautions (5.7)].

17.9 Serum Cholesterol and Triglyceride Elevation

Advise patients that elevations in total cholesterol, LDL and triglycerides may occur and that measurement of serum lipids may be considered [see Warnings and Precautions (5.8)].

17.10 Discontinuation

Advise patients not to stop taking PRISTIQ without talking first with their healthcare professional. Patients should be aware that discontinuation effects may occur when stopping PRISTIQ [see Warnings and Precautions (5.9) and Adverse Reactions (6.1)].

17.11 Switching Patients From Other Antidepressants to PRISTIQ

Discontinuation symptoms have been reported when switching patients from other antidepressants, including venlafaxine, to PRISTIQ. Tapering of the initial antidepressant may be necessary to minimize discontinuation symptoms.

17.12 Interference with Cognitive and Motor Performance

Caution patients about operating hazardous machinery, including automobiles, until they are reasonably certain that PRISTIQ therapy does not adversely affect their ability to engage in such activities.

17.13 Alcohol

Advise patients to avoid alcohol while taking PRISTIQ [see Drug Interactions (7.5)].

17.14 Allergic Reactions

Advise patients to notify their physician if they develop allergic phenomena such as rash, hives, swelling, or difficulty breathing.

17.15 Pregnancy

Advise patients to notify their physician if they become pregnant or intend to become pregnant during therapy [see Use in Specific Populations (8.1)].

17.16 Nursing

Advise patients to notify their physician if they are breastfeeding an infant [see Use in Specific Populations (8.3)].

17.17 Residual Inert Matrix Tablet

Patients receiving PRISTIQ may notice an inert matrix tablet passing in the stool or via colostomy. Patients should be informed that the active medication has already been absorbed by the time the patient sees the inert matrix tablet.

LAB-0452-5.0

Revised October 2011

Distributed by:
Physicians Total Care, Inc.
Tulsa, Oklahoma 74146

MEDICATION GUIDE

PRISTIQ® (pris-TEEK) Extended-Release Tablets

(desvenlafaxine)

Antidepressant Medicines, Depression and Other Serious Mental Illnesses, and Suicidal Thoughts or Actions

Read the Medication Guide that comes with your or your family member's antidepressant medicine. This Medication Guide is only about the risk of suicidal thoughts and actions with antidepressant medicines.

Talk to your, or your family member's, healthcare provider about:

- all risks and benefits of treatment with antidepressant medicines
- all treatment choices for depression or other serious mental illness

What is the most important information I should know about antidepressant medicines, depression and other serious mental illnesses, and suicidal thoughts or actions?

1. Antidepressant medicines may increase suicidal thoughts or actions in some children, teenagers, and young adults within the first few months of treatment.
2. Depression and other serious mental illnesses are the most important causes of suicidal thoughts and actions. Some people may have a particularly high risk of having suicidal thoughts or actions. These include people who have (or have a family history of) bipolar illness (also called manic-depressive illness) or suicidal thoughts or actions.
3. How can I watch for and try to prevent suicidal thoughts and actions in myself or a family member?

- Pay close attention to any changes, especially sudden changes, in mood, behaviors, thoughts, or feelings. This is very important when an antidepressant medicine is started or when the dose is changed.
- Call the healthcare provider right away to report new or sudden changes in mood, behavior, thoughts, or feelings.
- Keep all follow-up visits with the healthcare provider as scheduled. Call the healthcare provider between visits as needed, especially if you have concerns about symptoms.

Call a healthcare provider right away if you or your family member has any of the following symptoms, especially if they are new, worse, or worry you:

• thoughts about suicide or dying

• trouble sleeping (insomnia)

• attempts to commit suicide

• new or worse irritability

• new or worse depression

• acting aggressive, being angry, or violent

• new or worse anxiety

• acting on dangerous impulses

• feeling very agitated or restless

• an extreme increase in activity and talking (mania)

• panic attacks

• other unusual changes in behavior or mood

What else do I need to know about antidepressant medicines?

- Never stop an antidepressant medicine without first talking to a healthcare provider. Stopping an antidepressant medicine suddenly can cause other symptoms.
- Antidepressants are medicines used to treat depression and other illnesses. It is important to discuss all the risks of treating depression and also the risks of not treating it. Patients and their families or other caregivers should discuss all treatment choices with the healthcare provider, not just the use of antidepressants.
- Antidepressant medicines have other side effects. Talk to the healthcare provider about the side effects of the medicine prescribed for you or your family member.
- Antidepressant medicines can interact with other medicines. Know all of the medicines that you or your family member takes. Keep a list of all medicines to show the healthcare provider. Do not start new medicines without first checking with your healthcare provider.
- Not all antidepressant medicines prescribed for children are FDA approved for use in children. Talk to your child's healthcare provider for more information.

This Medication Guide has been approved by the U.S. Food and Drug Administration for all antidepressants.

Important Information about PRISTIQ® Extended-Release Tablets

Read the patient information that comes with PRISTIQ before you take PRISTIQ and each time you refill your prescription. There may be new information. If you have questions, ask your healthcare provider. This information does not take the place of talking with your healthcare provider about your medical condition or treatment.

What is PRISTIQ?

- PRISTIQ is a prescription medicine used to treat depression. PRISTIQ belongs to a class of medicines known as SNRIs (or serotonin-norepinephrine reuptake inhibitors).
- PRISTIQ has not been studied or approved for use in children and adolescents.

Do not take PRISTIQ if you:

- are allergic to desvenlafaxine, venlafaxine or any of the ingredients in PRISTIQ. See the end of this Medication Guide for a complete list of ingredients in PRISTIQ.
- currently take or have taken within the last 14 days, any medicine known as an MAOI. Taking an MAOI with certain other medicines, including PRISTIQ, can cause serious or even life-threatening side effects. Also, you must wait at least 7 days after you stop taking PRISTIQ before you take any MAOI.

What should I tell my healthcare provider before taking PRISTIQ?

Tell your healthcare provider about all your medical conditions, including if you:

- have high blood pressure
- have heart problems
- have high cholesterol or high triglycerides
- have a history of a stroke
- have or had depression, suicidal thoughts or behavior
- have glaucoma
- have kidney problems
- have liver problems
- have or had bleeding problems
- have or had seizures or convulsions
- have mania or bipolar disorder
- have low sodium levels in your blood
- are pregnant or plan to become pregnant. It is not known if PRISTIQ will harm your unborn baby.
- are breastfeeding. PRISTIQ can pass into your breast milk and may harm your baby. Talk with your healthcare provider about the best way to feed your baby if you take PRISTIQ.

Serotonin syndrome or neuroleptic malignant syndrome (NMS)-like reactions

Rare, but potentially life-threatening, conditions called serotonin syndrome or Neuroleptic Malignant Syndrome (NMS)-like reactions can happen when medicines such as PRISTIQ are taken with certain other medicines. Serotonin syndrome or NMS-like reactions can cause serious changes in how your brain, muscles, heart and blood vessels, and digestive system work. Especially tell your healthcare provider if you take the following:

- medicines to treat migraine headaches known as triptans
- medicines used to treat mood, anxiety, psychotic, or thought disorders, including tricyclics, lithium, selective serotonin reuptake inhibitors (SSRIs), serotonin norepinephrine reuptake inhibitors (SNRIs), antipsychotic drugs, or other dopamine antagonists, such as metoclopramide
- silbutramine
- tramadol
- St. John's Wort
- MAOIs (including linezolid, an antibiotic)
- tryptophan supplements

Ask your healthcare provider if you are not sure if you are taking any of these medicines.

Before you take PRISTIQ with any of these medicines, talk to your healthcare provider about serotonin syndrome. See “What are the possible side effects of PRISTIQ?”

PRISTIQ contains the medicine desvenlafaxine. Do not take PRISTIQ with other medicines containing venlafaxine or desvenlafaxine.

How should I take PRISTIQ?

- Take PRISTIQ exactly as your healthcare provider has told you.
- Take PRISTIQ at about the same time each day.
- PRISTIQ may be taken either with or without food.
- Swallow PRISTIQ tablets whole, with fluid. Do not crush, cut, chew, or dissolve PRISTIQ tablets because the tablets are time-released.
- When you take PRISTIQ, you may see something in your stool that looks like a tablet. This is the empty shell from the tablet after the medicine has been absorbed by your body.
- It is common for antidepressant medicines such as PRISTIQ to take several weeks before you start to feel better. Do not stop taking PRISTIQ if you do not feel results right away.
- Do not stop taking or change the dose of PRISTIQ without talking with your healthcare provider, even if you feel better.
- Talk with your healthcare provider about how long you should use PRISTIQ. Take PRISTIQ for as long as your healthcare provider tells you to.
- If you miss a dose of PRISTIQ, take it as soon as you remember. If it is almost time for your next dose, skip the missed dose. Do not try to “make up” for the missed dose by taking two doses at the same time.
- Do not take more PRISTIQ than prescribed by your healthcare provider. If you take more PRISTIQ than the amount prescribed, contact your healthcare provider right away.
- In case of an overdose of PRISTIQ, call your healthcare provider or poison control center, or go to the emergency room right away.

Switching from other antidepressants

Side effects from discontinuing antidepressant medication have occurred when patients switched from other antidepressants, including venlafaxine, to PRISTIQ. Your doctor may gradually reduce the dose of your initial antidepressant medication to help to reduce these side effects.

What should I avoid while taking PRISTIQ?

- Do not drive a car or operate machinery until you know how PRISTIQ affects you.
- Avoid drinking alcohol while taking PRISTIQ.

PRISTIQ can cause serious side effects, including:

- See the beginning of this Medication Guide - Antidepressant Medicines, Depression and other Serious Mental Illnesses, and Suicidal Thoughts or Actions.
- Serotonin syndrome or neuroleptic malignant syndrome (NMS)-like reactions. See “What should I tell my healthcare provider before taking PRISTIQ?”
  Get medical help right away if you think that you have these syndromes. Signs and symptoms of these syndromes may include one or more of the following:

• restlessness

• increase in blood pressure

• hallucinations (seeing and hearing things that are not real)

• diarrhea

• loss of coordination

• coma

• fast heart beat

• nausea

• increased body temperature

• vomiting

• muscle stiffness

• confusion

PRISTIQ may also cause other serious side effects, including:

- New or worsened high blood pressure (hypertension). Your healthcare provider should monitor your blood pressure before and while you are taking PRISTIQ. If you have high blood pressure, it should be controlled before you start taking PRISTIQ.
- Abnormal bleeding or bruising. PRISTIQ and other SNRIs/SSRIs may cause you to have an increased chance of bleeding. Taking aspirin, NSAIDs (non-steroidal anti-inflammatory drugs), or blood thinners may add to this risk. Tell your healthcare provider right away about any unusual bleeding or bruising.
- Glaucoma (increased eye pressure)
- Increased cholesterol and triglyceride levels in your blood
- Symptoms when stopping PRISTIQ (discontinuation symptoms). Side effects may occur when stopping PRISTIQ (discontinuation symptoms), especially when therapy is stopped suddenly. Your healthcare provider may want to decrease your dose slowly to help avoid side effects. Some of these side effects may include:

• dizziness

• anxiety

• nausea

• abnormal dreams

• headache

• tiredness

• irritability

• sweating

• sleeping problems (insomnia)

• diarrhea

- Seizures (convulsions)
- Low sodium levels in your blood. Symptoms of this may include: headache, difficulty concentrating, memory changes, confusion, weakness and unsteadiness on your feet. In severe or more sudden cases, symptoms can include: hallucinations (seeing or hearing things that are not real), fainting, seizures and coma. If not treated, severe low sodium levels could be fatal.
- Allergic reactions. Some reactions can be severe such as swelling beneath the skin (e.g., throat, face, hands).

Contact your healthcare provider if you think you have any of these side effects.

Common side effects with PRISTIQ include:

• nausea

• tiredness

• headache

• diarrhea

• dry mouth

• vomiting

• sweating

• anxiety

• dizziness

• tremor

• insomnia

• dilated pupils

• constipation

• decreased sex drive

• loss of appetite

• delayed orgasm and ejaculation

• sleepiness

• feeling that your surroundings are spinning or moving

These are not all the possible side effects of PRISTIQ. Tell your healthcare provider about any side effect that bothers you or does not go away. Call your doctor for medical advice about side effects. You may report side effects to FDA at 1-800-FDA-1088. For more information on these and other side effects associated with PRISTIQ, talk to your healthcare provider, visit our web site at www.pristiq.com or call our toll-free number at 1‑888‑PRISTIQ (774‑7847).

How should I store PRISTIQ?

- Store PRISTIQ at 68° to 77°F (20° to 25°C).
- Do not use PRISTIQ after the expiration date (EXP), which is on the container. The expiration date refers to the last day of that month.
- Keep PRISTIQ and all medicines out of the reach of children.

General Information about the safe and effective use of PRISTIQ

Medicines are sometimes used for conditions that are not mentioned in Medication Guides. Do not use PRISTIQ for a condition for which it was not prescribed. Do not give PRISTIQ to other people, even if they have the same symptoms that you have. It may harm them.

This Medication Guide summarizes the most important information about PRISTIQ. If you would like more information, talk with your healthcare provider. You can ask your pharmacist or healthcare provider for information about PRISTIQ that is written for healthcare professionals. For more information, go to www.pristiq.com or call 1‑888‑PRISTIQ (774‑7847).

What are the ingredients in PRISTIQ?

Active ingredient: desvenlafaxine

Inactive ingredients: For the 50 mg tablet, hypromellose, microcrystalline cellulose, talc, magnesium stearate and film coating, which consists of polyvinyl alcohol, polyethylene glycol, talc, titanium dioxide, and iron oxides.

For the 100 mg tablet, hypromellose, microcrystalline cellulose, talc, magnesium stearate, a film coating which consists of polyvinyl alcohol, polyethylene glycol, talc, titanium dioxide, iron oxide and FD&C yellow #6.

This Medication Guide has been approved by the U.S. Food and Drug Administration.

Issued April 2011.

Contact Information

Please visit our web site at www.pristiq.com, or call our toll-free number 1-888-PRISTIQ (774-7847) to receive more information.

This product's label may have been updated. For current package insert and further product information, please visit www.wyeth.com or call our medical communications department toll-free at 1‑800‑934‑5556.

LAB-0539-2.0

Revised July 2011

PACKAGE LABEL – PRINCIPAL DISPLAY PANEL – 50 MG LABEL

NDC 54868-2932-0

Pristiq™

desvenlafaxine

Extended-Release Tablets

50 mg

Note: Give attached Medication Guide when dispensing Pristiq™.

Rx only